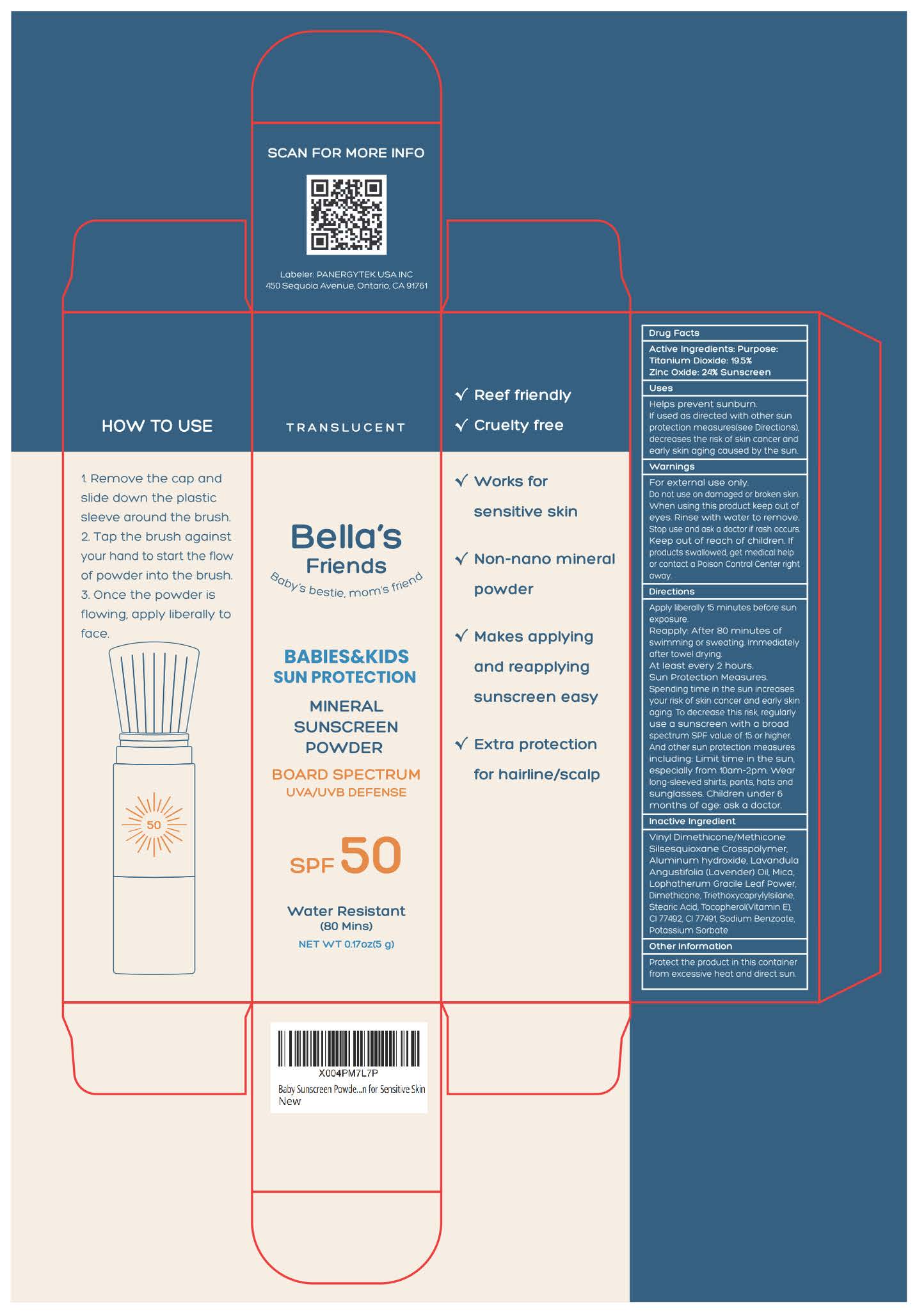 DRUG LABEL: BABIES KIDSSUN PROTECTION
NDC: 85950-001 | Form: POWDER
Manufacturer: PANERGYTEK USA INC
Category: otc | Type: HUMAN OTC DRUG LABEL
Date: 20250801

ACTIVE INGREDIENTS: ZINC OXIDE 240 mg/1 g; TITANIUM DIOXIDE 195 mg/1 g
INACTIVE INGREDIENTS: VINYL DIMETHICONE/METHICONE SILSESQUIOXANE CROSSPOLYMER; POTASSIUM SORBATE; MICA; CI 77491; LAVANDULA ANGUSTIFOLIA (LAVENDER) OIL; TRIETHOXYCAPRYLYLSILANE; STEARIC ACID; TOCOPHEROL; LOPHATHERUM GRACILE LEAF; ALUMINUM HYDROXIDE; CI 77492; SODIUM BENZOATE

ACTIVE INGREDIENT

Titanium dioxide-19.5%

Zinc oxide-24%

PURPOSE

Sunscreen

WHEN USING

Helps prevent sunburn.If used as directed with other sunprotection measures(see Directions)decreases the risk of skin cancer andearly skin aging caused by the sun.

WARNINGS

For external use only.Do not use on damaged or broken skinWhen using this product keep out ofeyes. Rinse with water to remove.Stop use and ask a doctor if rash occursKeep out of reach of children. lfproducts swallowed. get medical helpor contact a Poison Control Center rightaway.

DOSAGE AND ADMINISTRATION

Apply liberally 15 minutes before sunexposure.
Reapply: After 80 minutes ofswimming or sweating. immediatelyafter towel drying.At least every 2 hours.Sun Protection Measures.Spending time in the sun increasesyour risk of skin cancer and early skinaging. To decrease this risk, regularlyuse a sunscreen with a broadspectrum SPF value of 15 or higher.And other sun protection measuresincluding: Limit time in the sun,especially from 10am-2pm. wearlong-sleeved shirts, pants, hats andsunglasses. Children under 6months of age: ask a doctor

INDICATIONS AND USAGE

Apply liberally 15 minutes before sunexposure.
Reapply: After 80 minutes ofswimming or sweating. immediatelyafter towel drying.At least every 2 hours.Sun Protection Measures.Spending time in the sun increasesyour risk of skin cancer and early skinaging. To decrease this risk, regularlyuse a sunscreen with a broadspectrum SPF value of 15 or higher.And other sun protection measuresincluding: Limit time in the sun,especially from 10am-2pm. wearlong-sleeved shirts, pants, hats andsunglasses. Children under 6months of age: ask a doctor

Keep out of reach of children. If swallowed, get medical help or contact a Poison Control Center right away.

OTHER SAFETY INFORMATION

Protect this product in this container from excessive heat and direct sun.

INACTIVE INGREDIENT

Vinyl Dimethicone/MethiconeSilsesquioxane Crosspolymer.

Aluminum hydroxide.

LavandulaAngustifolia (Lavender) Oil,

Mica.

Lophatherum Gracile Leaf Power,

Dimethicone,

Triethoxycoprylylsilane

.Stearic Acid,

Tocopherol(Vitamin E),

C1 77492,

C1 77491

Sodium Benzoate

,Potassium Sorbate